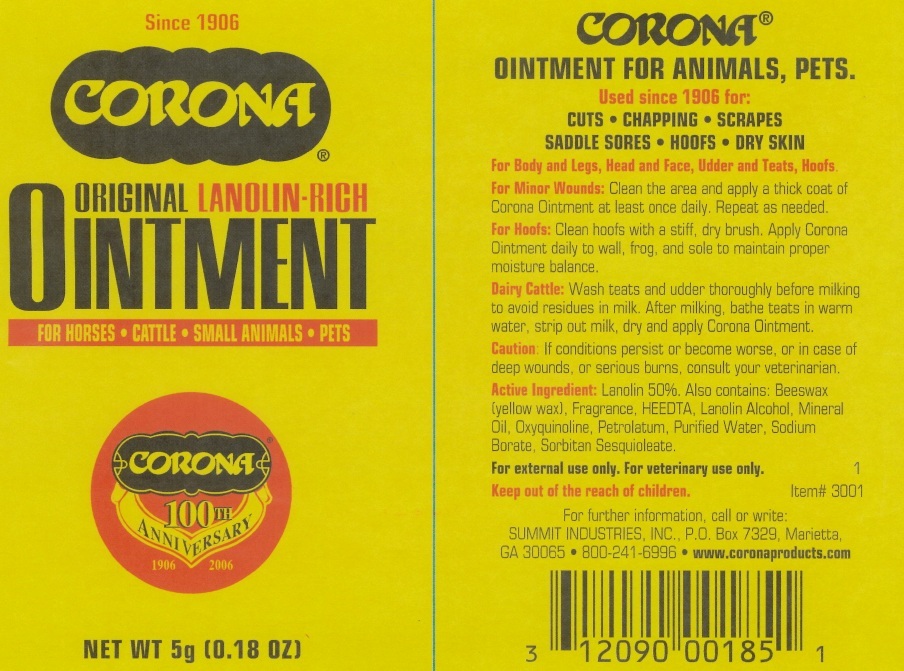 DRUG LABEL: CORONA ORIGINAL LANOLIN RICH
NDC: 12090-0030 | Form: OINTMENT
Manufacturer: SUMMIT INDUSTRIES, INC.
Category: animal | Type: OTC ANIMAL DRUG LABEL
Date: 20101104

ACTIVE INGREDIENTS: LANOLIN 50 g/100 g
INACTIVE INGREDIENTS: YELLOW WAX; MINERAL OIL; OXYQUINOLINE; PETROLATUM; WATER; SODIUM BORATE; SORBITAN SESQUIOLEATE

CORONA ORIGINAL LANOLIN-RICH OINTMENT

Active Ingredient: Lanolin...50%

PURPOSE

Cuts, chapping, scrapes, saddle sores, hoofs, dry skin

DOSAGE AND ADMINISTRATION

For Body and Legs, head and face, Udder and Teats, Hoofs
For minor wounds: clean the area and apply a thick coat of Corona Ointment at least once daily. Repeat as needed.
For Hoofs: clean hoofs with a stiff, dry brush. Apply Corona Ointment daily to wall frog, and sol to maintain proper moisture balance.
Dairy Cattle: Wash teats and udder thoroughly before milking to avoid residues in milk. After milking, bathe teats in warm water, strip out milk, dry, and apply Corona Ointment

WARNINGS

Caution: if conditions persist or become worse, or in case of deep wounds, or serious burns, consult your veterinarian.

INACTIVE INGREDIENT

Also contains: Beeswax (yellow wax), Fragrance, HEEDTA, Lanolin Alcohol, Mineral Oil, Oxyquinoline, Petrolatum, Purified Water, Sodium Borate, Sorbitan Sesquioleate

Keep out of reach of children

DESCRIPTION

Corona

Ointment for animals, pets

Used since 1906 for:

cuts, chapping, scrapes, saddle sores, hoofs, dry skin

For external use only. For veterinary use only.

For further information call or write:

SUMMIT INDUSTRIES, INC.

PO BOX 7329 MARIETTA, GA 30065

800-241-6996

www.coronaproducts.com